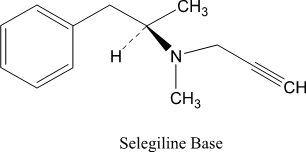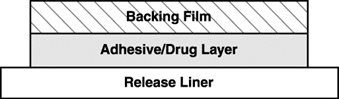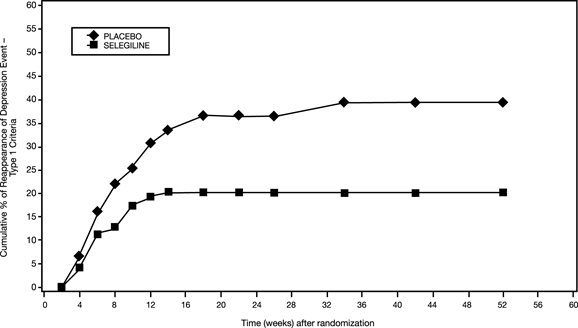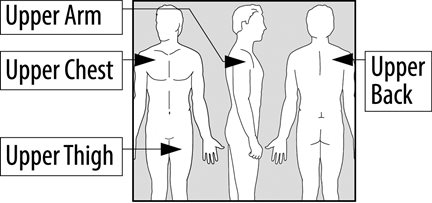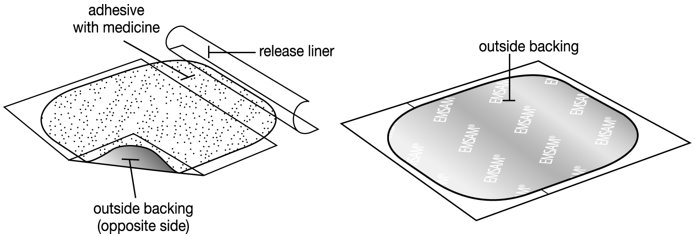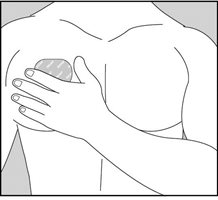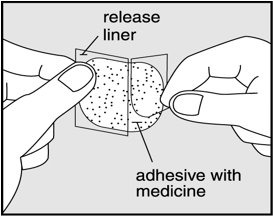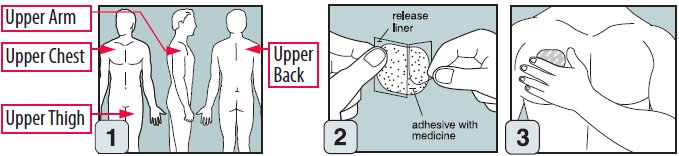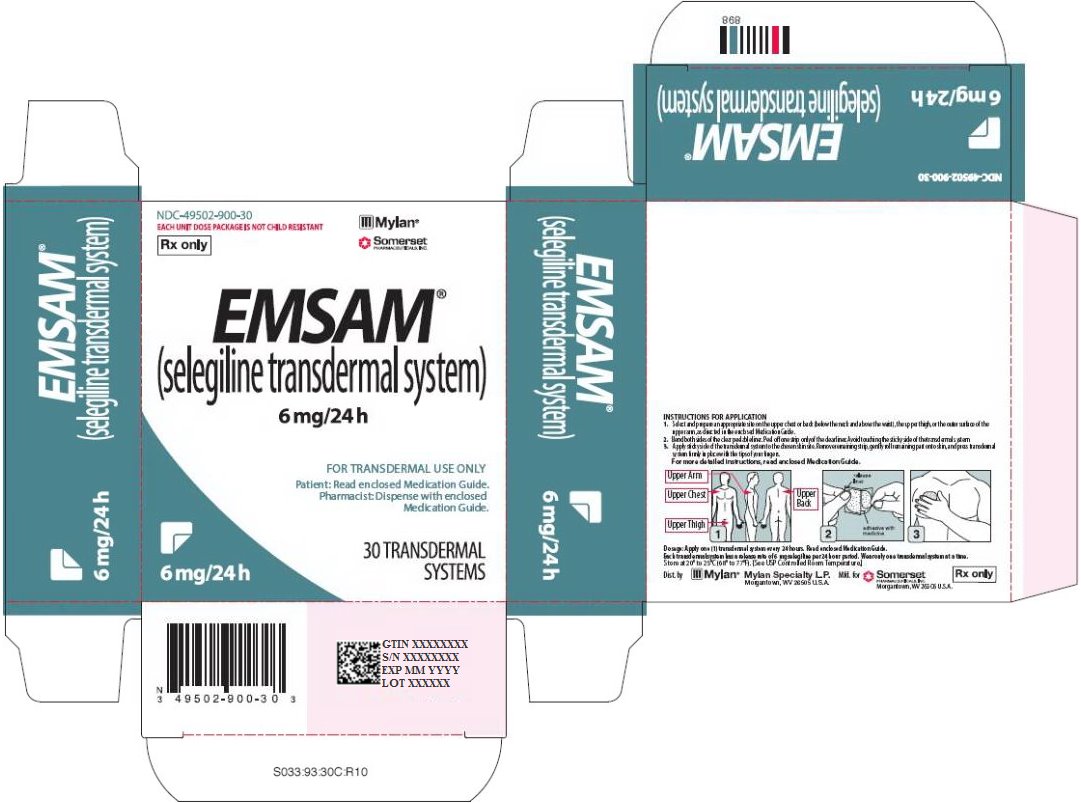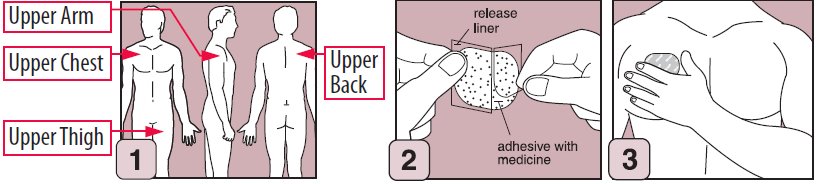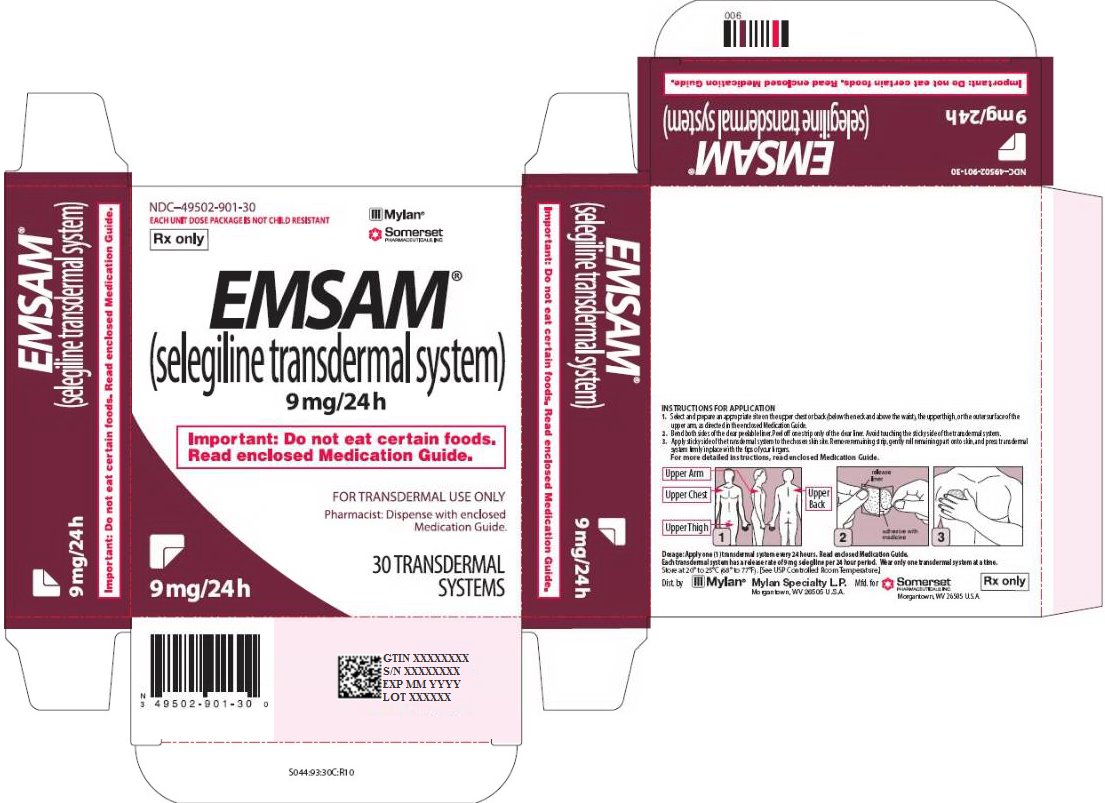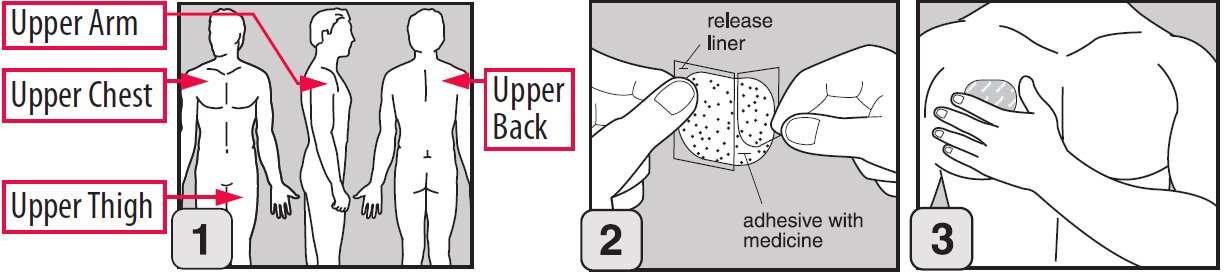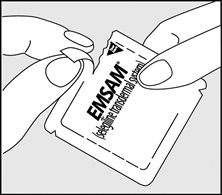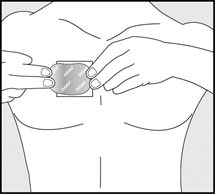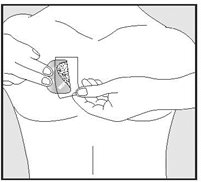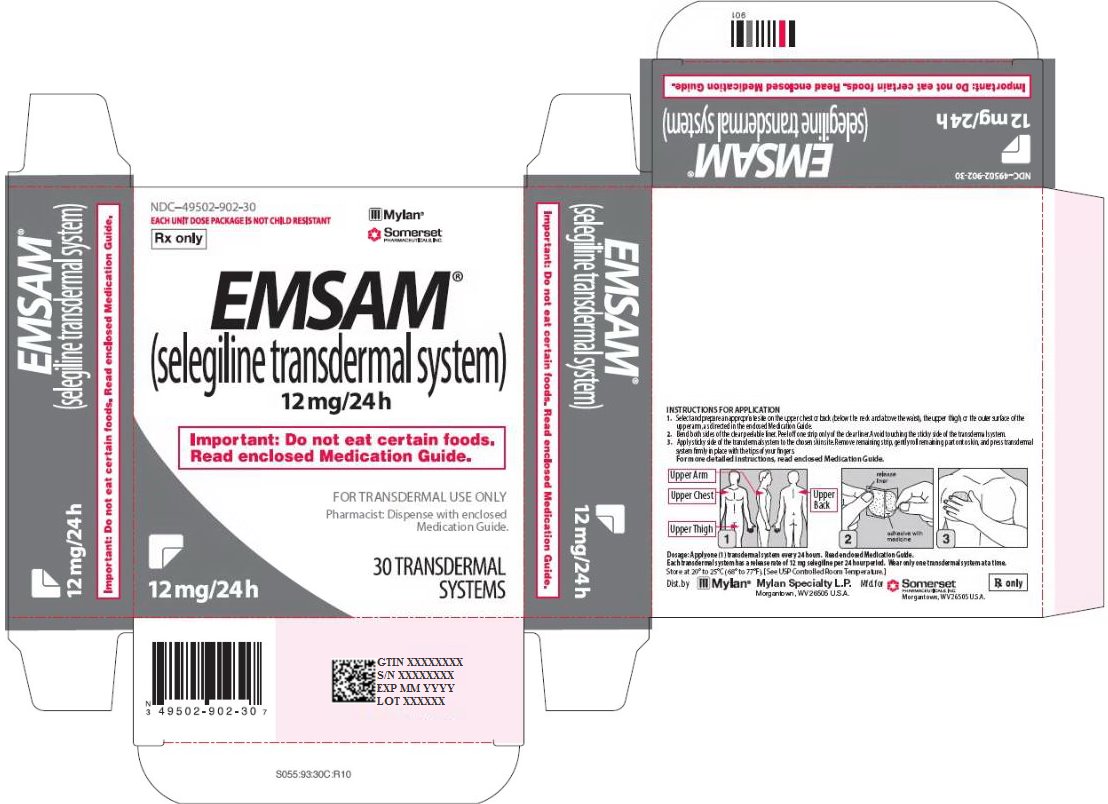 DRUG LABEL: EMSAM
NDC: 49502-900 | Form: PATCH
Manufacturer: Viatris Specialty LLC
Category: prescription | Type: HUMAN PRESCRIPTION DRUG LABEL
Date: 20200515

ACTIVE INGREDIENTS: SELEGILINE 6 mg/24 h

HIGHLIGHTS OF PRESCRIBING INFORMATION

These highlights do not include all the information needed to use EMSAM safely and effectively. See full prescribing information for EMSAM.
EMSAM® (selegiline transdermal system)
Initial U.S. Approval: 2006

WARNING: SUICIDAL THOUGHTS AND BEHAVIORS

See full prescribing information for complete boxed warning.

- Increased risk of suicidal thoughts and behaviors in pediatric and young adult patients taking antidepressants. Closely monitor all antidepressant-treated patients for clinical worsening and emergence of suicidal thoughts and behaviors (5.1).
- EMSAM is contraindicated in patients less than 12 years of age (4, 8.4).

1 INDICATIONS AND USAGE

EMSAM® (selegiline transdermal system) is a monoamine oxidase inhibitor (MAOI) indicated for the treatment of major depressive disorder (MDD) (1).

2 DOSAGE AND ADMINISTRATION

EMSAM should be applied to dry, intact skin on the upper torso (below the neck and above the waist), upper thigh or the outer surface of the upper arm once every 24 hours (2.1).

- Initial Treatment: The recommended starting dose and target dose for EMSAM is 6 mg per 24 hours (2.1).
Based on clinical judgment, dose increases should occur in increments of 3 mg per 24 hours (up to a maximum dose of 12 mg per 24 hours) at intervals of no less than 2 weeks (2.1).
- Geriatric Use: The recommended dose for elderly patients (65 years and older) is EMSAM 6 mg per 24 hours daily (8.5).
- Dietary Modifications with EMSAM 9 mg per 24 hours and 12 mg per 24 hours: Tyramine-rich foods and beverages should be avoided beginning on the first day of EMSAM 9 mg per 24 hours or 12 mg per 24 hours treatment, and should continue to be avoided for 2 weeks after a dose reduction to EMSAM 6 mg per 24 hours or following the discontinuation of EMSAM 9 mg per 24 hours or 12 mg per 24 hours (2.3).

3 DOSAGE FORMS AND STRENGTHS

Transdermal System: 6 mg per 24 hours, 9 mg per 24 hours and 12 mg per 24 hours (3).

4 CONTRAINDICATIONS

- Serotonergic drugs: selective serotonin reuptake inhibitors (SSRIs), serotonin and norepinephrine reuptake inhibitors (SNRIs), clomipramine and imipramine, meperidine, tramadol, methadone, pentazocine, and propoxyphene; and the antitussive agent dextromethorphan should not be used with EMSAM because of a risk of serotonin syndrome (4, 5.2).
- Carbamazepine should not be used with EMSAM (4, 5.3).
- After stopping treatment with contraindicated medication, a time period equal to 4 to 5 half-lives (approximately one week) of the drug or any active metabolite should elapse before starting therapy with EMSAM. Because of the long half-life of fluoxetine and its active metabolite, at least 5 weeks should elapse between discontinuation of fluoxetine and initiation of treatment with EMSAM (4).
- At least 2 weeks should elapse after stopping EMSAM before starting therapy with a drug that is contraindicated with EMSAM (4).
- EMSAM is contraindicated in patients less than 12 years of age (4, 8.4).
- Pheochromocytoma (4).

5 WARNINGS AND PRECAUTIONS

- Tyramine-Induced Hypertensive Crisis: Patients receiving EMSAM 9 mg per 24 hours and 12 mg per 24 hours should follow the recommended dietary modifications (5.3).
- Blood Pressure Elevation Related to Concomitant Medication: monitor blood pressure if EMSAM is used with any of the following drugs: buspirone, amphetamines, or cold products or weight-reducing preparations that contain sympathomimetic amines (e.g., pseudoephedrine, phenylephrine, phenylpropanolamine, and ephedrine). If a hypertensive crisis occurs, EMSAM should be discontinued immediately and therapy to lower blood pressure should be instituted immediately (5.3).
- Activation of Mania/Hypomania: Screen patients for bipolar disorder (5.4).
- External Heat: Avoid exposing the EMSAM application site to external sources of direct heat, such as heating pads or electric blankets, heat lamps, saunas, hot tubs, heated water beds, and prolonged direct sunlight (5.5).

6 ADVERSE REACTIONS

- Adverse Reactions occurring at an incidence of 2% or More Among EMSAM-Treated Patients and greater than placebo: Application site reaction, headache, insomnia, diarrhea, dry mouth, dyspepsia, rash, pharyngitis, sinusitis (6.1).

To report SUSPECTED ADVERSE REACTIONS, contact Mylan at 1-877-4-INFO-RX (1-877-446-3679) or FDA at 1-800-FDA-1088 or www.fda.gov/medwatch.

8 USE IN SPECIFIC POPULATIONS

- Pregnancy: May cause fetal harm (8.1).
- Lactation: Breastfeeding is not recommended (8.2).
- Pediatrics: EMSAM is contraindicated in patients under age 12 years and is not recommended in patients 12 to 17 years of age (4, 8.4).

FULL PRESCRIBING INFORMATION

WARNING: SUICIDAL THOUGHTS AND BEHAVIORS

Antidepressants increased the risk of suicidal thoughts and behaviors in pediatric and young adult patients in short-term studies. Closely monitor all antidepressant-treated patients for clinical worsening, and for emergence of suicidal thoughts and behaviors [see Warnings and Precautions (5.1)].

EMSAM is contraindicated in patients less than 12 years of age because of an increased risk of hypertensive crisis [see Contraindications (4) and Use in Specific Populations (8.4)].

1 INDICATIONS AND USAGE

EMSAM (selegiline transdermal system) is a monoamine oxidase inhibitor (MAOI) indicated for the treatment of adults with major depressive disorder (MDD) [see Clinical Studies (14)].

2 DOSAGE AND ADMINISTRATION

2.1 Initial Treatment

EMSAM should be applied to dry, intact skin on the upper torso (below the neck and above the waist), upper thigh or the outer surface of the upper arm once every 24 hours. The recommended starting dose and target dose for EMSAM is 6 mg per 24 hours. EMSAM has been systematically evaluated and shown to be effective in a dose range of 6 mg per 24 hours to 12 mg per 24 hours. However, the trials were not designed to assess if higher doses are more effective than the lowest effective dose of 6 mg per 24 hours. Based on clinical judgment, if dose increases are indicated for individual patients, they should occur in dose increments of 3 mg per 24 hours (up to a maximum dose of 12 mg per 24 hours) at intervals of no less than 2 weeks. Full antidepressant effect may be delayed.

Patients should be informed that tyramine-rich foods and beverages should be avoided beginning on the first day of EMSAM 9 mg per 24 hours or 12 mg per 24 hours treatment and should continue to be avoided for 2 weeks after a dose reduction to EMSAM 6 mg per 24 hours or following the discontinuation of EMSAM 9 mg per 24 hours or 12 mg per 24 hours [see Warnings and Precautions (5.3)].

2.2 Maintenance Treatment

It is generally agreed that episodes of depression require several months or longer of sustained pharmacologic therapy. Maintenance of efficacy in depressed patients on therapy with EMSAM at a dose of 6 mg per 24 hours after achieving a responder status for an average duration of about 25 days was demonstrated in a controlled trial [see Clinical Studies (14)].

The physician who elects to use EMSAM for extended periods should periodically re-evaluate the long-term usefulness of the drug for the individual patient.

2.3 Dietary Modifications Required for Patients Taking EMSAM 9 mg per 24 hours and 12 mg per 24 hours

EMSAM (selegiline transdermal system) contains a monoamine oxidase inhibitor (MAOI). MAOIs including EMSAM combined with a high tyramine diet may cause a hypertensive crisis. A hypertensive crisis can be a life-threatening condition [see Warnings and Precautions (5.3)].

The foods and beverages listed in Table 5 should be avoided beginning on the first day of EMSAM 9 mg per 24 hours or 12 mg per 24 hours treatment, and should continue to be avoided for 2 weeks after a dose reduction to EMSAM 6 mg per 24 hours or following the discontinuation of EMSAM 9 mg per 24 hours or 12 mg per 24 hours [see Drug Interactions (7.2)].

2.4 Screen for Bipolar Disorder Prior to Starting EMSAM

Prior to initiating treatment with EMSAM or another antidepressant, screen patients for a personal or family history of bipolar disorder, mania, or hypomania [see Warnings and Precautions (5.4)].

3 DOSAGE FORMS AND STRENGTHS

EMSAM (selegiline transdermal system) is supplied as 6 mg per 24 hours (20 mg per 20 cm^2), 9 mg per 24 hours (30 mg per 30 cm^2) and 12 mg per 24 hours (40 mg per 40 cm^2) transdermal systems (TDS).

EMSAM 6 mg per 24 hours is a translucent TDS printed with ‘EMSAM® 6mg/24h’. EMSAM 9 mg per 24 hours is a translucent TDS printed with ‘EMSAM® 9mg/24h’. EMSAM 12 mg per 24 hours is a translucent TDS printed with ‘EMSAM® 12mg/24h’.

4 CONTRAINDICATIONS

- EMSAM (selegiline transdermal system) is contraindicated with selective serotonin reuptake inhibitors (SSRIs, e.g., fluoxetine, sertraline, and paroxetine); serotonin and norepinephrine reuptake inhibitors (SNRIs, e.g., venlafaxine and duloxetine); the tricyclic antidepressants clomipramine and imipramine, the opiate analgesics meperidine, tramadol, methadone, pentazocine, and propoxyphene; and the antitussive agent dextromethorphan because of a risk of serotonin syndrome when EMSAM is used with these agents [see Warnings and Precautions (5.2) and Drug Interactions (7.1)].
- Carbamazepine is contraindicated with EMSAM because of a possible increased risk of hypertensive crisis [see Warnings and Precautions (5.3) and Clinical Pharmacology (12.3)].
- After stopping treatment with drugs contraindicated with EMSAM, a time period equal to 4 to 5 half-lives (approximately one week) of the drug or any active metabolite should elapse before starting therapy with EMSAM. Because of the long half-life of fluoxetine and its active metabolite, at least 5 weeks should elapse between discontinuation of fluoxetine and initiation of treatment with EMSAM.
- At least 2 weeks should elapse after stopping EMSAM before starting therapy with any drug that is contraindicated with EMSAM.
- EMSAM is contraindicated in patients less than 12 years of age because of the potential for a hypertensive crisis [see Use in Specific Populations (8.4) and Clinical Pharmacology (12.3)].
- EMSAM is contraindicated in patients with pheochromocytoma because MAOIs may precipitate a hypertensive crisis in such patients.

5 WARNINGS AND PRECAUTIONS

5.1 Suicidal Thoughts and Behaviors in Adolescents and Young Adults

In pooled analyses of placebo-controlled trials of antidepressant drugs (SSRIs and other antidepressant classes) that included approximately 77,000 adult patients and over 4,400 pediatric patients, the incidence of suicidal thoughts and behaviors in pediatric and young adult patients was greater in antidepressant-treated patients than in placebo-treated patients. The drug-placebo differences in the number of cases of suicidal thoughts and behaviors per 1000 patients treated are provided in Table 1.

No suicides occurred in any of the pediatric studies. There were suicides in the adult studies, but the number was not sufficient to reach any conclusion about antidepressant drug effect on suicide.

Table 1: Risk Differences of the Number of Cases of Suicidal Thoughts or Behaviors in the Pooled Placebo-Controlled Trials of Antidepressants in Pediatric and Adult Patients
Age Range (years) | Drug-Placebo Difference in Number of Patients of Suicidal Thoughts or Behaviors per 1000 Patients Treated
 | Increases Compared to Placebo
<18 | 14 additional patients
18-24 | 5 additional patients
 | Decreases Compared to Placebo
25-64 | 1 fewer patient
≥65 | 6 fewer patients

It is unknown whether the risk of suicidal thoughts and behaviors in pediatric and young adult patients extends to longer-term use, i.e., beyond four months. However, there is substantial evidence from placebo-controlled maintenance trials in adults with MDD that antidepressants delay the recurrence of depression.

Monitor all antidepressant-treated patients for clinical worsening and emergence of suicidal thoughts and behaviors, especially during the initial few months of drug therapy and at times of dosage changes. Counsel family members or caregivers of patients to monitor for changes in behavior and to alert the healthcare provider. Consider changing the therapeutic regimen, including possibly discontinuing EMSAM, in patients whose depression is persistently worse, or who are experiencing emergent suicidal thoughts or behaviors.

5.2 Serotonin Syndrome

The development of a potentially life-threatening serotonin syndrome has been reported with concomitant use of MAOIs, such as EMSAM, with serotonergic drugs. These reactions have also been reported in patients who have discontinued serotonergic drugs and then subsequently started an MAOI [see Contraindications (4)].

Serotonin syndrome symptoms may include mental status changes (e.g., agitation, hallucinations, delirium, and coma), autonomic instability (e.g., tachycardia, labile blood pressure, dizziness, diaphoresis, flushing, hyperthermia), neuromuscular changes (e.g., tremor, rigidity, myoclonus, hyperreflexia, incoordination), seizures, and/or gastrointestinal symptoms (e.g., nausea, vomiting, diarrhea).

Patients should be monitored for the emergence of serotonin syndrome. Treatment with EMSAM and any concomitant serotonergic agents should be discontinued immediately if the above events occur and supportive treatment should be initiated.

5.3 Blood Pressure Elevation

Tyramine-Induced Hypertensive Crisis

EMSAM inhibits the catabolism of dietary amines, such as tyramine, and has the potential to produce a hypertensive crisis following the ingestion of tyramine-rich foods or beverages [see Drug Interactions (7.2) and Clinical Pharmacology (12.2)].

Hypertensive crises, which in some cases may be fatal, are characterized by some or all of the following symptoms: occipital headache which may radiate frontally, palpitation, neck stiffness or soreness, nausea, vomiting, sweating (sometimes with fever and sometimes with cold, clammy skin), dilated pupils, and photophobia. Either tachycardia or bradycardia may be present and can be associated with constricting chest pain. Intracranial bleeding has been reported in association with the increase in blood pressure. Patients should be instructed as to the signs and symptoms of severe hypertension and advised to seek immediate medical attention if these signs or symptoms are present.

If a hypertensive crisis occurs, EMSAM should be discontinued immediately and therapy to lower blood pressure should be instituted immediately. Fever should be managed by means of external cooling. Patients must be closely monitored until symptoms have stabilized. To prevent a hypertensive crisis, patients receiving treatment with EMSAM 9 mg per 24 hours or EMSAM 12 mg per 24 hours should follow the advice regarding a low tyramine diet described in Table 5 under Dietary Modifications Required for Patients Taking EMSAM 9 mg per 24 hours and 12 mg per 24 hours [see Drug Interactions (7.2)].

Blood Pressure Elevation Related to Concomitant Medication

Carbamazepine is contraindicated with EMSAM because carbamazepine has been shown to significantly elevate selegiline levels, which may increase the risk of a hypertensive crisis [see Contraindications (4) and Drug Interactions (7.4)].

The use of EMSAM with adrenergic drugs or buspirone may produce substantial increases in blood pressure. Therefore, monitor blood pressure if EMSAM is used with any of the following drugs: buspirone, amphetamines, or cold products or weight-reducing preparations that contain sympathomimetic amines (e.g., pseudoephedrine, phenylephrine, phenylpropanolamine, and ephedrine).

5.4 Activation of Mania/Hypomania

In patients with bipolar disorder, treating a depressive episode with EMSAM or another antidepressant may precipitate a mixed/manic episode. During Phase III trials, a manic reaction occurred in 8 out of 2,036 (0.4%) patients treated with EMSAM. Prior to initiating treatment with EMSAM, screen patients for any personal or family history of bipolar disorder, mania, or hypomania.

5.5 External Heat

The effect of direct heat applied to EMSAM on the bioavailability of selegiline has not been studied. However, in theory, heat may result in an increase in the amount of selegiline absorbed from EMSAM and produce elevated serum levels of selegiline. Patients should be advised to avoid exposing the EMSAM application site to external sources of direct heat, such as heating pads or electric blankets, heat lamps, saunas, hot tubs, heated water beds, and prolonged direct sunlight.

6 ADVERSE REACTIONS

The following adverse reactions are discussed in greater detail in other sections of the label.

- Suicidal Thoughts and Behaviors [see Warnings and Precautions (5.1)].
- Serotonin Syndrome [see Contraindications (4) and Warnings and Precautions (5.2)].
- Blood Pressure Elevation [see Warnings and Precautions (5.3)].
- Activation of Mania/Hypomania [see Warnings and Precautions (5.4)].
- External Heat [see Warnings and Precautions (5.5)].

6.1 Clinical Trial Experience

Because clinical trials are conducted under widely varying conditions, adverse reaction rates observed in the clinical trials of a drug cannot be directly compared to rates in the clinical trials of another drug and may not reflect the rates observed in clinical practice.

Patient Exposure

The premarketing development program for EMSAM included selegiline exposures in patients and/or normal subjects from two different groups of studies: 702 healthy subjects in clinical pharmacology/pharmacokinetics studies and 2,036 exposures from patients in controlled and uncontrolled major depressive disorder clinical trials. The conditions and duration of treatment with EMSAM varied and included double-blind, open-label, fixed-dose, and dose titration studies of short-term and longer-term exposures. Safety was assessed by monitoring adverse reactions, physical examinations, vital signs, body weights, laboratory analyses, and ECGs.

Adverse reactions during exposure were obtained primarily by general inquiry and recorded by clinical investigators. In the tables and tabulations that follow, standard COSTART terminology has been used to classify reported adverse reactions. The stated frequencies of adverse reactions represent the proportion of individuals who experienced, at least once, a treatment-emergent adverse reaction of the type listed. A reaction was considered treatment-emergent if it occurred for the first time or worsened while receiving therapy following baseline evaluation.

Adverse Reactions Leading To Discontinuation of Treatment

Among 817 MDD patients treated with EMSAM at doses of either 3 mg per 24 hours (151 patients), 6 mg per 24 hours (550 patients) or 6 mg per 24 hours, 9 mg per 24 hours, and 12 mg per 24 hours (116 patients) in placebo-controlled trials of up to 8 weeks in duration, 7.1% discontinued treatment due to an adverse reaction as compared with 3.6% of 668 patients receiving placebo. The only adverse reaction associated with discontinuation, in at least 1% of EMSAM-treated patients at a rate at least twice that of placebo, was application site reaction (2% EMSAM vs. 0% placebo).

Adverse Reactions Occurring at an Incidence of 2% or More Among EMSAM-Treated Patients

Table 2 enumerates adverse reactions that occurred at an incidence of 2% or more (rounded to the nearest percent) among 817 MDD patients treated with EMSAM in doses ranging from 3 to 12 mg per 24 hours in placebo-controlled trials of up to 8 weeks in duration. Reactions included are those occurring in 2% or more of patients treated with EMSAM and for which the incidence in patients treated with EMSAM was greater than the incidence in placebo-treated patients.

One adverse reaction was associated with a reporting of at least 5% in the EMSAM group, and a rate at least twice that in the placebo group, in the pool of short-term, placebo-controlled studies: application site reactions (see Application Site Reactions, below). In one such study which utilized higher mean doses of EMSAM than that in the entire study pool, the following reactions met these criteria: application site reactions, insomnia, diarrhea, and pharyngitis.

Table 2. Treatment-Emergent Adverse Reactions: Incidence in Placebo-Controlled Clinical Trials for Major Depressive Disorder with EMSAM [Reactions reported by at least 2% of patients treated with EMSAM are included, except the following reactions, which had an incidence on placebo treatment greater than or equal to EMSAM: infection, nausea, dizziness, pain, abdominal pain, nervousness, back pain, asthenia, anxiety, flu syndrome, accidental injury, somnolence, rhinitis, and palpitations.]
Body System/Preferred Term | EMSAM; (N = 817) | Placebo; (N = 668)
 | (% of Patients Reporting Reaction)
Body as a Whole
Headache | 18 | 17
Digestive
Diarrhea | 9 | 7
Dyspepsia | 4 | 3
Nervous
Insomnia | 12 | 7
Dry Mouth | 8 | 6
Respiratory
Pharyngitis | 3 | 2
Sinusitis | 3 | 1
Skin
Application Site Reaction | 24 | 12
Rash | 4 | 2

Application Site Reactions

In the pool of short-term, placebo-controlled major depressive disorder studies, application site reactions (ASRs) were reported in 24% of EMSAM-treated patients and 12% of placebo-treated patients. Most ASRs were mild or moderate in severity. ASRs led to dropout in 2% of EMSAM-treated patients and no placebo-treated patients. In one such study which utilized higher mean doses of EMSAM, ASRs were reported in 40% of EMSAM-treated patients and 20% of placebo-treated patients. Most of the ASRs in this study were described as erythema and most resolved spontaneously, requiring no treatment. When treatment was administered, it most commonly consisted of dermatological preparations of corticosteroids.

Sexual Dysfunction

Although changes in sexual desire, sexual performance, and sexual satisfaction often occur as manifestations of a psychiatric disorder, they may also be a consequence of pharmacologic treatment.

Reliable estimates of the incidence and severity of untoward experiences involving sexual desire, performance, and satisfaction are difficult to obtain, in part because patients and physicians may be reluctant to discuss them. Accordingly, estimates of the incidence of untoward sexual experience and performance cited in product labeling are likely to underestimate their actual incidence. Table 3 shows that the incidence rates of sexual side effects in patients with major depressive disorder are comparable to the placebo rates in placebo-controlled trials.

Table 3. Incidence of Sexual Side Effects in Placebo-Controlled Clinical Trials with EMSAM
Adverse Reaction | EMSAM | Placebo
 | IN MALES ONLY
 | (N = 304) | (N = 256)
Abnormal Ejaculation | 1.0% | 0.0%
Decreased Libido | 0.7% | 0.0%
Impotence | 0.7% | 0.4%
Anorgasmia | 0.2% | 0.0%
 | IN FEMALES ONLY
 | (N = 513) | (N = 412)
Decreased Libido | 0.0% | 0.2%

There are no adequately designed studies examining sexual dysfunction with EMSAM treatment.

Vital Sign Changes

EMSAM and placebo groups were compared with respect to (1) mean change from baseline in vital signs (pulse, systolic blood pressure, and diastolic blood pressure), and (2) the incidence of patients meeting criteria for potentially clinically significant changes from baseline in these variables. In the pool of short-term, placebo-controlled major depressive disorder studies, 3.0% of EMSAM-treated patients and 1.5% of placebo-treated patients experienced a low systolic blood pressure, defined as a reading less than or equal to 90 mmHg with a change from baseline of at least 20 mmHg. In one study which utilized higher mean doses of EMSAM, 6.2% of EMSAM-treated patients and no placebo-treated patients experienced a low standing systolic blood pressure by these criteria.

In the pool of short-term major depressive disorder trials, 9.8% of EMSAM-treated patients and 6.7% of placebo-treated patients experienced a notable orthostatic change in blood pressure, defined as a decrease of at least 10 mmHg in mean blood pressure with postural change.

Weight Changes

In placebo-controlled studies (6 to 8 weeks), the incidence of patients who experienced at least 5% weight gain or weight loss is shown in Table 4.

Table 4. Incidence of Weight Gain and Weight Loss in Placebo-Controlled Trials with EMSAM
Weight Change | EMSAM | Placebo
 | (N = 757) | (N = 614)
Gained at least 5% | 2.1% | 2.4%
Lost at least 5% | 5.0% | 2.8%

In these trials, the mean change in body weight among EMSAM-treated patients was a 1.2 lbs loss compared to 0.3 lbs gain in placebo-treated patients.

Laboratory Changes

EMSAM and placebo groups were compared with respect to (1) mean change from baseline in various serum chemistry, hematology, and urinalysis variables, and (2) the incidence of patients meeting criteria for potentially clinically significant changes from baseline in these variables. These analyses revealed no clinically important changes in laboratory test parameters associated with EMSAM.

Electrocardiogram Changes

Electrocardiograms (ECGs) from EMSAM (N = 817) and placebo (N = 668) groups in controlled studies were compared with respect to (1) mean change from baseline in various ECG parameters, and (2) the incidence of patients meeting criteria for clinically significant changes from baseline in these variables.

No clinically meaningful changes in ECG parameters from baseline to final visit were observed for patients in controlled studies.

Other Reactions Observed During the Premarketing Evaluation of EMSAM

The following listing does not include reactions: 1) already listed elsewhere in labeling, 2) for which a causal relationship to drug was remote, 3) which were so general as to be uninformative, 4) which were not considered to have significant clinical implications, or 5) which occurred at a rate equal to or less than placebo.

Cardiovascular System: Tachycardia.

Digestive System: Anorexia.

Nervous System: Agitation, amnesia, tremor, twitching.

Skin and Appendages: Pruritus.

6.2 Postmarketing Experience

The following adverse reactions have been identified during post-approval use of EMSAM.

Because these reactions are reported voluntarily from a population of uncertain size, it is not always possible to reliably estimate their frequency or establish a causal relationship to drug exposure.

Nervous System: Convulsion and hypoesthesia.

Psychiatric System: Disorientation, hallucination (visual), and tension.

7 DRUG INTERACTIONS

7.1 Serotonergic Drugs

Serious, sometimes fatal, central nervous system (CNS) toxicity referred to as the “serotonin syndrome” has been reported with the combination of nonselective MAOIs and serotonergic drugs. Use of EMSAM with these drugs is contraindicated [see Contraindications (4) and Warnings and Precautions (5.2)].

7.2 Tyramine

EMSAM has the capacity to inhibit intestinal MAO, which is responsible for the catabolism of tyramine in food and beverages. As a result of this inhibition, large amounts of tyramine may enter the systemic circulation and precipitate a sudden, large rise in blood pressure or hypertensive crisis [see Warnings and Precautions (5.3) and Clinical Pharmacology (12.2)].

A diet low in tyramine content may be necessary to avoid this interaction. Studies to evaluate the potential for EMSAM to inhibit tyramine metabolism have been conducted and, overall, the data for EMSAM 6 mg per 24 hours support a recommendation that a modified diet is not required at this dose. Due to the more limited data available for EMSAM 9 mg per 24 hours and the results from the Phase I tyramine challenge study in fed volunteers administered EMSAM 12 mg per 24 hours, patients receiving these doses should follow Dietary Modifications Required for Patients Taking EMSAM 9 mg per 24 hours and 12 mg per 24 hours below [see Clinical Pharmacology (12.2)].

Dietary Modifications Required for Patients Taking EMSAM 9 mg per 24 hours and 12 mg per 24 hours

The foods and beverages listed in Table 5 should be avoided beginning on the first day of EMSAM 9 mg per 24 hours or 12 mg per 24 hours treatment, and should continue to be avoided for 2 weeks after a dose reduction to EMSAM 6 mg per 24 hours or following the discontinuation of EMSAM 9 mg per 24 hours or 12 mg per 24 hours.

Table 5. Food and Beverages to Avoid and Those which are Acceptable [[see References (15)]]
Class of Food and Beverage | Tyramine-Rich Foods and Beverages to Avoid | Acceptable Foods and Drinks,; Containing No or Little Tyramine
Meat, Poultry, and Fish | Air dried, aged and fermented meats, sausages and salamis (including cacciatore, hard salami and mortadella); pickled herring; and any spoiled or improperly stored meat, poultry, and fish (e.g., foods that have undergone changes in coloration, odor, or become moldy); spoiled or improperly stored animal livers | Fresh meat, poultry, and fish, including fresh processed meats (e.g., lunch meats, hot dogs, breakfast sausage, and cooked sliced ham)
Vegetables | Broad bean pods (fava bean pods) | All other vegetables
Dairy | Aged cheeses | Processed cheeses, mozzarella, ricotta cheese, cottage cheese, and yogurt
Beverages | All varieties of tap beer and beers that have not been pasteurized so as to allow for ongoing fermentation | Concomitant use of alcohol with EMSAM is not recommended. (Bottled and canned beers and wines contain little or no tyramine.)
Miscellaneous | Concentrated yeast extract (e.g., Marmite), sauerkraut, most soybean products (including soy sauce and tofu), OTC supplements containing tyramine | Brewer’s yeast, baker’s yeast, soy milk, commercial chain restaurant pizzas prepared with cheeses low in tyramine

7.3 Sympathomimetic Amines and Buspirone

The use of EMSAM with sympathomimetic amines or buspirone may produce substantial elevations in blood pressure. Therefore, monitor blood pressure if EMSAM is used with any of the following drugs: buspirone, amphetamines, and cold products or weight-reducing preparations that contain sympathomimetic amines (e.g., pseudoephedrine, phenylephrine, phenylpropanolamine, and ephedrine).

7.4 Effect of Other Drugs on EMSAM

Carbamazepine is contraindicated with MAOIs, including selegiline [see Contraindications (4), Warnings and Precautions (5.3) and Clinical Pharmacology (12.3)].

No dose adjustment for EMSAM is needed when EMSAM is used concomitantly with alcohol, alprazolam, ibuprofen, olanzapine, risperidone, levothyroxine, and CYP3A4 inhibitors (e.g., ketoconazole). No clinically meaningful change in selegiline exposure was seen when EMSAM was co-administered with alcohol, alprazolam, ibuprofen, olanzapine, risperidone, levothyroxine, and ketoconazole [see Clinical Pharmacology (12.3)].

7.5 Effect of EMSAM on Other Drugs

Use of alcohol while taking EMSAM is not recommended, even though EMSAM has not been shown to increase the impairment of mental and motor skills caused by alcohol (0.75 mg per kg) [see Clinical Pharmacology (12.3)].

Monitor blood pressure if sympathomimetic agents (e.g., phenylpropanolamine (PPA) or pseudoephedrine) are used with EMSAM, even though selegiline does not appear to affect the pharmacokinetics of PPA or pseudoephedrine [see Clinical Pharmacology (12.3)].

No dose adjustment of alprazolam, ibuprofen, levothyroxine, olanzapine, risperidone, warfarin, or strong CYP3A4 inhibitors (e.g., ketoconazole) is necessary when these drugs are used in combination with EMSAM. EMSAM had no clinically relevant effect on pharmacokinetics of these drugs.

8 USE IN SPECIFIC POPULATIONS

8.1 Pregnancy

Risk Summary

The available data on EMSAM use in pregnant women are not sufficient to inform a drug-associated risk of adverse pregnancy-related outcomes. In animal embryo-fetal development studies, transdermal administration of selegiline to rats and rabbits at doses up to 60 and 64 times the maximum recommended human dose (MRHD) respectively, produced slight increases in malformations in both rats and rabbits, and decreased fetal weight, delayed ossification, and embryo-fetal post-implantation loss in rats. Most of these effects were seen at the high dose in both rats and rabbits. These effects were not seen at 8 times and 16 times the MRHD in rats and rabbits, respectively. In a pre-natal and post-natal development study, transdermal administration of selegiline in rats at doses 8, 24, and 60 times MRHD produced a decrease in pup weight and survival at the medium and high doses, an increase in the number of stillborn pups at the high dose, and delayed neurobehavioral and sexual development in pups

at all doses. A persistent effect on reproductive performance of pups born to mothers treated at the high dose was evident (see Data). When treating a pregnant woman with EMSAM, the physician should carefully consider both the potential risks of taking an MAOI, particularly the risk of hypertensive crisis during pregnancy, along with the established benefits of treating depression with an antidepressant.

The estimated background risk of major birth defects and miscarriage for the indicated population is unknown. All pregnancies have a background risk of birth defect, loss, or other adverse outcomes. In the U.S. general population, the estimated background risk of major birth defects and miscarriage in clinically recognized pregnancies is 2% to 4% and 15% to 20%, respectively.

Clinical Considerations

Disease-associated maternal and embryo/fetal risk

A prospective longitudinal study was conducted of 201 pregnant women with a history of major depression, who were either on antidepressants or had received antidepressants less than 12 weeks prior to their last menstrual period, and were in remission. Women who discontinued antidepressant medication during pregnancy showed a significant increase in relapse of their major depression compared to those women who remained on antidepressant medication throughout pregnancy.

Data

Animal Data

In an embryofetal development study, rats were treated with transdermal selegiline during the period of organogenesis at doses of 10, 30, and 75 mg/kg/day (8, 24, and 60 times the MRHD of EMSAM [12 mg/24 hours] on a mg/m^2 basis). At the highest dose there was a decrease in fetal weight and slight increases in malformations, delayed ossification (also seen at the mid dose), and embryofetal post-implantation loss. Concentrations of selegiline and its metabolites in fetal plasma were generally similar to those in maternal plasma.

In an embryofetal development study, rabbits were treated with transdermal selegiline during the period of organogenesis at doses of 2.5, 10, and 40 mg/kg/day (4, 16, and 64 times the MRHD on a mg/m^2 basis). A slight increase in visceral malformations was seen at the high dose.

In a prenatal and postnatal development study, rats were treated with transdermal selegiline at doses of 10, 30, and 75 mg/kg/day (8, 24, and 60 times the MRHD on a mg/m^2 basis) on days 6 to 21 of gestation and days 1 to 21 of the lactation period. An increase in post-implantation loss was seen at the mid and high doses, and an increase in stillborn pups was seen at the high dose. Decreases in pup weight (throughout lactation and postweaning periods) and survival (throughout lactation period), delayed pup physical development, and pup epididymal and testicular hypoplasia, were seen at the mid and high doses. Delayed neurobehavioral and sexual development was seen at all doses. Adverse effects on pup reproductive performance, as evidenced by decreases in implantations and litter size, were seen at the high dose. These findings suggest persistent effects on the offspring of treated dams. A no-effect dose was not established in this study for developmental toxicity.

8.2 Lactation

Risk Summary

There is no information regarding the presence of selegiline in human milk, or on its effects on milk production or the breastfed infant. Selegiline and its metabolites are present in the milk of lactating rats (see Data).

Because of the potential for serious adverse reactions in breastfed infants from EMSAM, including the potential for hypertensive crisis, advise a woman that breastfeeding is not recommended during treatment with EMSAM and for 5 days after the final dose.

Data

In a prenatal and postnatal development study where rats were treated with transdermal selegiline at doses approximately 8, 24, and 60 times the MRHD on days 6 to 21 of gestation and days 1 to 21 of the lactation period, concentrations of selegiline and its metabolites in milk were approximately 15 and 5 times, respectively, the concentrations in maternal plasma.

8.4 Pediatric Use

Use of EMSAM in patients less than 12 years of age is contraindicated because of the potential for a hypertensive crisis [see Contraindications (4)].

Limited pharmacokinetic data with doses lower than in the commercially available formulations suggest that children under age 12 may be exposed to increased levels of selegiline compared to adolescents and adults, administered with and without dietary modifications, therefore, there may be an increased risk of hypertensive crisis, even at the lowest dose of EMSAM.

Efficacy has not been established in pediatric patients ages 12 to 17 years with MDD and EMSAM is not recommended for use in this age range [see Clinical Pharmacology (12.3)].

A multi-center, randomized, double-blind, placebo-controlled, flexible-dose trial in 308 adolescents (ages 12 to 17 years) with MDD failed to demonstrate the efficacy of EMSAM. Diagnosis of major depressive disorder (single episode or recurrent, moderate to severe) was based on according DSM-IV criteria and Kiddie Schedule for Affective Disorders and Schizophrenia for School Aged Children (K-SADS). Enrolled patients had a Children’s Depression Rating Scale-Revised of ≥ 45 at the screening visit. Trial participants were randomized 1:1 to either EMSAM or matching placebo without forced titration for a period of 12 weeks. Active treatment consisted of EMSAM transdermal system at a dose of 6 mg per 24 hours, 9 mg per 24 hours, or 12 mg per 24 hours. The primary efficacy endpoint was the difference in total score on the Children’s Depression Rating Scale-Revised (CDRS-R) from baseline to the end of study (EOS) (Week 12). There was no observed difference in effect on CDRS-R Total Score at Week 12 (EOS) between treatments. The mean reduction in CDRS-R Total Score was 21.4 in the EMSAM-treated subjects and 21.5 in those receiving placebo treatment. Safety endpoints included physical examination, 12-lead electrocardiogram, respiration rate, temperature, supine and standing blood pressure and heart rate, application site assessments, and adverse events. Overall, safety findings were similar to those observed in EMSAM trials conducted in adults. Treatment-emergent adverse events reported by at least 5% of EMSAM-treated patients at a rate at least twice the placebo rate were insomnia (6%, 3%) and upper respiratory tract infection (7%, 3%).

8.5 Geriatric Use

The recommended dose of EMSAM for elderly patients (65 years and older) is 6 mg per 24 hours daily. The effect of age on the pharmacokinetics or metabolism of selegiline after administration of EMSAM has not been systematically evaluated. One hundred ninety-eight (198) elderly (65 years of age and older) patients participated in clinical studies with EMSAM 6 mg per 24 hours to 12 mg per 24 hours. There were no overall differences in effectiveness between elderly and younger patients. In short-term, placebo-controlled depression trials, patients age 50 and older appeared to be at higher risk for rash (4.4% EMSAM vs. 0% placebo) than younger patients (3.4% EMSAM vs. 2.4% placebo).

8.6 Gender

No adjustment of EMSAM dosage based on gender is needed. No gender differences have been observed in the pharmacokinetics or metabolism of selegiline during administration of EMSAM.

8.7 Reduced Hepatic Function

No adjustment of EMSAM dosage is required in patients with mild liver impairment (Child-Pugh 5-6 points) or moderate liver impairment (Child-Pugh 7-9 points). After a single administration of EMSAM 6 mg per 24 hours in eight patients with mild or moderate liver impairment, no differences in either the metabolism or pharmacokinetic behavior of selegiline or its metabolites were observed as compared with data of normal subjects. EMSAM has not been studied in patients with severe liver impairment (Child-Pugh 10-15 points).

8.8 Reduced Renal Function

No adjustment of EMSAM dosage is required in patients with mild renal impairment (eGFR 60-89 mL/min/1.73 m^2), moderate renal impairment (eGFR 30-59 mL/min/1.73 m^2), or severe renal impairment (eGFR 15-29 mL/min/1.73 m^2). Data from a single dose study examining the pharmacokinetics of EMSAM 6 mg per 24 hours in 12 patients with renal impairment suggest that mild, moderate, or severe renal impairment does not affect the pharmacokinetics of selegiline after transdermal application. EMSAM has not been studied in patients with end-stage renal disease (eGFR < 15 mL/min/1.73 m^2 or requiring dialysis).

9 DRUG ABUSE AND DEPENDENCE

EMSAM is not a controlled substance.

10 OVERDOSAGE

10.1 Signs and Symptoms

EMSAM overdosage may resemble overdosage with other nonselective, oral MAOI antidepressants and present with any of the following: drowsiness, dizziness, faintness, irritability, hyperactivity, agitation, severe headache, hallucinations, trismus, opisthotonos, convulsions, coma, rapid and irregular pulse, hypertension, hypotension and vascular collapse, precordial pain, respiratory depression and failure, hyperpyrexia, diaphoresis, and cool, clammy skin.

10.2 Management of Overdose

There are no specific antidotes for EMSAM.

If symptoms of overdosage occur, immediately remove the EMSAM system and institute appropriate supportive therapy. For contemporary information on the management of poisoning or overdosage, contact the National Poison Control Center at 1-800-222-1222.

Delays of up to 12 hours between ingestion of drug and the appearance of signs may occur, and peak effects may not be observed for 24 to 48 hours. Since death has been reported following overdosage with MAOI agents, hospitalization with close monitoring during this period is strongly recommended.

In order to avoid the occurrence of hypertensive crisis (“cheese reaction”), dietary tyramine should be restricted for several weeks beyond recovery to permit regeneration of the peripheral MAO-A isoenzyme.

11 DESCRIPTION

EMSAM® contains selegiline, a MAOI antidepressant. When applied to intact skin, EMSAM is designed to transdermally deliver selegiline over a 24-hour period.

Selegiline base is a colorless to yellow liquid, chemically described as (-)-(N)-Methyl-N-[(1R)-1-methyl-2-phenylethyl]prop-2-yn-1-amine. It has a molecular formula of C13H17N and a molecular weight of 187.30. The structural formula is:

EMSAM transdermal systems are available in three strengths that deliver approximately 6 mg, 9 mg, or 12 mg of selegiline over 24 hours. Each corresponding system has an active surface area of 20 cm^2, 30 cm^2, or 40 cm^2 containing 20, 30, or 40 mg of selegiline, respectively. The composition of the systems per unit area is identical.

EMSAM is a matrix-type transdermal system composed of three layers as illustrated in Figure 1 below. Layer 1 is the Backing Film that provides occlusivity, physical integrity and protects the adhesive/drug layer. Layer 2 is the Adhesive/Drug Layer. Layer 3 consists of side-by-side release liners that are peeled off and discarded by the patient prior to applying EMSAM. The inactive ingredients are acrylic adhesive, ethylene vinyl acetate/polyethylene, polyester, polyurethane, and silicone coated polyester.

Figure 1: Side view of EMSAM system. (Not to scale.)

12 CLINICAL PHARMACOLOGY

12.1 Mechanism of Action

The mechanism of action of selegiline (the drug substance of EMSAM) as an antidepressant is not fully understood, but is presumed to be linked to potentiation of monoamine neurotransmitter activity in the central nervous system (CNS) resulting from its irreversible inhibition of the enzyme monoamine oxidase (MAO).

12.2 Pharmacodynamics

MAO exists as two isoenzymes, referred to as MAO-A and MAO-B. Selegiline has a greater affinity for MAO-B, compared to MAO-A. However, at antidepressant doses, selegiline inhibits both isoenzymes. In an in vivo animal model used to test for antidepressant activity (Forced Swim Test), selegiline administered by transdermal system exhibited antidepressant properties only at doses that inhibited both MAO-A and MAO-B activity in the brain. In the CNS, MAO-A and MAO-B play important roles in the catabolism of neurotransmitter amines such as norepinephrine, dopamine, and serotonin, as well as neuromodulators such as phenylethylamine.

Receptor Binding

In in vitro receptor binding assays, selegiline has demonstrated affinity for the human recombinant adrenergic α2B receptor (Ki = 0.3 mcM). No affinity [Ki greater than 10 mcM] was noted at dopamine receptors, adrenergic β3, glutamate, muscarinic M1-M5, nicotinic, or rolipram receptor/sites.

Interaction with Tyramine

Selegiline (the drug substance of EMSAM) is an irreversible inhibitor of monoamine oxidase (MAO), a ubiquitous intracellular enzyme. MAO exists as two isoenzymes, referred to as MAO-A and MAO-B. Selegiline shows greater affinity for MAO-B; however, as selegiline concentration increases, this selectivity is lost with resulting dose-related inhibition of MAO-A. Intestinal MAO is predominantly type A, while in the brain both isoenzymes exist.

MAO plays a vital physiological role in terminating the biological activity of both endogenous and exogenous amines. In addition to their role in the catabolism of monoamines in the CNS, MAOs are also important in the catabolism of exogenous amines found in a variety of foods and drugs. MAO in the gastrointestinal tract (primarily type A) provides protection from exogenous amines with vasopressor actions, such as tyramine, which if absorbed intact can cause a hypertensive crisis, the so-called “cheese reaction”. If a large amount of tyramine is absorbed systemically, it is taken up by adrenergic neurons and causes norepinephrine release from neuronal storage sites with resultant elevation of blood pressure. While most foods contain negligible amounts or no tyramine, certain food products may contain large amounts of tyramine that represent a potential risk for hypertensive crisis [see Warnings and Precautions (5.3)].

To define the risk of hypertensive crises with use of EMSAM, several Phase I tyramine challenge studies were conducted both with and without food. Fourteen tyramine challenge studies including 214 healthy subjects (age range 18 to 65; 31 subjects greater than 50 years of age) were conducted to determine the pressor effects of oral tyramine with concurrent EMSAM treatment (6 mg per 24 hours to 12 mg per 24 hours), measured as the dose of tyramine required to raise systolic blood pressure by 30 mmHg (TYR30). Studies were conducted with and without concomitant administration of food. Studies conducted with food are most relevant to clinical practice since tyramine typically will be consumed in food. A high-tyramine meal is considered to contain up to 40 mg of tyramine.

One study using a crossover design in 13 subjects investigated tyramine pressor doses (TYR30) after administration of EMSAM 6 mg per 24 hours and oral selegiline (5 mg twice daily) for 9 days. Mean pressor doses (TYR30) of tyramine capsules administered without food were 338 mg and 385 mg in subjects treated with EMSAM and oral selegiline, respectively.

Another study using a crossover design in 10 subjects investigated tyramine pressor doses after administration of EMSAM 6 mg per 24 hours or tranylcypromine 30 mg per day for 10 days. Mean pressor doses (TYR30) of tyramine capsules administered without food were 270 mg in subjects treated with EMSAM 6 mg per 24 hours and 10 mg in subjects treated with tranylcypromine.

In a third crossover study, tyramine without food was administered to 12 subjects. The mean tyramine pressor doses (TYR30) after administration of EMSAM 6 mg per 24 hours for 9 and 33 days were 292 mg and 204 mg, respectively. The lowest pressor dose was 50 mg in one subject in the 33-day group.

Tyramine pressor doses were also studied in 11 subjects after extended treatment with EMSAM 12 mg per 24 hours. At 30, 60, and 90 days, the mean pressor doses (TYR30) of tyramine administered without food were 95 mg, 72 mg, and 88 mg, respectively. The lowest pressor dose without food was 25 mg in three subjects at day 30 while on EMSAM 12 mg per 24 hours. Eight subjects from this study, with a mean tyramine pressor dose of 64 mg at 90 days, were subsequently administered tyramine with food, resulting in a mean pressor dose of 172 mg (2.7 times the mean pressor dose observed without food, p less than 0.003).

With the exception of one study (N = 153), the Phase III clinical development program was conducted without requiring a modified diet (N = 2,553, 1,606 at 6 mg per 24 hours, and 947 at 9 mg per 24 hours or 12 mg per 24 hours). No hypertensive crises were reported in any patient receiving EMSAM.

Overall, the data for EMSAM 6 mg per 24 hours support a recommendation that a modified diet is not required at this dose. Due to the more limited data available for EMSAM 9 mg per 24 hours and the results from the Phase I tyramine challenge study in fed volunteers administered EMSAM 12 mg per 24 hours, patients receiving these doses should follow Dietary Modifications Required for Patients Taking EMSAM 9 mg per 24 hours and 12 mg per 24 hours [see Warnings and Precautions (5.3)].

12.3 Pharmacokinetics

Absorption

Following dermal application of EMSAM to humans, 25% to 30% of the selegiline content on average is delivered systemically over 24 hours (range approximately 10% to 40%). Consequently, the degree of drug absorption may be 1/3 higher than the average amounts of 6 mg to 12 mg per 24 hours. Transdermal dosing results in significantly higher exposure to selegiline with significantly lower exposure for all metabolites when compared to oral dosing, due to extensive first-pass metabolism. In a 10-day study with daily administration of EMSAM to healthy male and female volunteers, steady-state selegiline plasma concentrations indicated selegiline concentration-time profiles were comparable when EMSAM is applied to the upper torso or upper thigh, and absorption from these two sites of administration was equivalent.

Distribution

Following dermal application of radiolabeled selegiline to laboratory animals, selegiline is rapidly distributed to all body tissues. Selegiline rapidly penetrates the blood-brain barrier.

In humans, selegiline is approximately 90% bound to plasma protein over a 2 to 500 ng per mL concentration range. Selegiline does not accumulate in the skin.

In vivo Metabolism

Transdermally absorbed selegiline (via EMSAM) is not metabolized in human skin and does not undergo extensive first-pass metabolism. Selegiline is extensively metabolized by several CYP450-dependent enzyme systems (see In vitro Metabolism). Selegiline is metabolized initially via N-dealkylation or N-depropargylation to form N-desmethylselegiline or R(-)-methamphetamine, respectively. Both of these metabolites can be further metabolized to R(-)-amphetamine. These metabolites are all levorotatory (l-)enantiomers and no racemic biotransformation to the dextrorotatory form (i.e., S(+)-amphetamine or S(+)-methamphetamine) occurs. R(-)-methamphetamine and R(-)-amphetamine are mainly excreted unchanged in urine.

In vitro Metabolism

In vitro studies utilizing human liver microsomes demonstrated that several CYP450-dependent enzymes are involved in the metabolism of selegiline and its metabolites. CYP2B6, CYP2C9, CYP3A4 and CYP3A5 appeared to be the major contributing enzymes in the formation of R(-)-methamphetamine from selegiline, with CYP2A6 having a minor role. CYP2A6, CYP2B6, CYP3A4 and CYP3A5 appeared to contribute to the formation of R(-)-amphetamine from N-desmethylselegiline.

The potential for selegiline or N-desmethylselegiline to inhibit individual CYP450-dependent enzyme pathways was also examined in vitro with human liver microsomes. Each substrate was examined over a concentration range of 2.5 to 250 mcM. Consistent with competitive inhibition, both selegiline and N-desmethylselegiline caused a concentration dependent inhibition of CYP2D6 at 10 to 250 mcM and CYP3A4 and CYP3A5 at 25 to 250 mcM. CYP2C19 and CYP2B6 were also inhibited at concentrations of 100 mcM or greater. All inhibitory effects of selegiline and N-desmethylselegiline occurred at concentrations that are several orders of magnitude higher than concentrations seen clinically (highest predose concentration observed at a dose of 12 mg per 24 hours at steady-state was 0.046 mcM) [see Drug Interactions (7)].

Excretion

Approximately 10% and 2% of a radiolabeled dose applied dermally, as a DMSO solution, was recovered in urine and feces respectively, with at least 63% of the dose remaining unabsorbed. The remaining 25% of the dose was unaccounted for. Urinary excretion of unchanged selegiline accounted for 0.1% of the applied dose with the remainder of the dose recovered in urine being metabolites.

The systemic clearance of selegiline after intravenous administration was 1.4 L per min, and the mean half-lives of selegiline and its three metabolites, R(-)-N-desmethylselegiline, R(-)-amphetamine, and R(-)-methamphetamine, ranged from 18 to 25 hours.

Population Subgroups

Age

EMSAM should not be used in patients less than 18 years of age [see Use in Specific Populations (8.4)].

Stratification of exposure data following treatment with EMSAM indicated that pre-dose (trough) selegiline plasma concentrations at steady state appeared higher (p = 0.12) in children aged < 12 years old, compared to adolescents aged ≥ 12 years as shown in Table 6.

Table 6. Steady State Selegiline Trough Concentrations Associated with Administration of EMSAM 15 mg/15 cm^2 Daily for 7 Days
Trough Concentration, pg/mL
 | 6 to 11 year old age group | 12 to 14 year old age group
 | (N = 6) | (N = 4)
Mean (SD) | 2,562 (974) | 1,821 (146)

Drug-Drug Interactions

Alcohol

The pharmacokinetics and pharmacodynamics of alcohol (0.75 mg per kg) alone or in combination with EMSAM 6 mg per 24 hours for 7 days of treatment was examined in 16 healthy volunteers. No clinically significant differences were observed in the pharmacokinetics or pharmacodynamics of alcohol or the pharmacokinetics of selegiline during co-administration. Although EMSAM has not been shown to increase the impairment of mental and motor skills caused by alcohol (0.75 mg per kg) and failed to alter the pharmacokinetic properties of alcohol, patients should be advised that the use of alcohol is not recommended while taking EMSAM [see Drug Interactions (7.4) and (7.5)].

Alprazolam

In subjects who had received EMSAM 6 mg per 24 hours for 7 days, co-administration with alprazolam (15 mg per day), a CYP3A4 and CYP3A5 substrate, did not affect the pharmacokinetics of alprazolam or selegiline [see Drug Interactions (7.4) and (7.5)].

Carbamazepine

Carbamazepine is an enzyme inducer and typically causes decreases in drug exposure; however, approximately 2-fold increased systemic exposure of selegiline and its metabolites, L-amphetamine and L-methamphetamine were seen after single application of EMSAM 6 mg per 24 hours in subjects who had received carbamazepine (400 mg per day) for 14 days. Changes in plasma selegiline concentrations were nearly 2-fold and variable across the subject population. Such increases may increase the risk of a hypertensive crisis when carbamazepine is used with EMSAM at any dose [see Contraindications (4), Warnings and Precautions (5.3) and Drug Interaction (7.4)].

Ibuprofen

In subjects who had received EMSAM 6 mg per 24 hours for 11 days, combined administration with the CYP2C9 substrate ibuprofen (800 mg single dose) did not affect the pharmacokinetics of either selegiline or ibuprofen [see Drug Interactions (7.4) and (7.5)].

Ketoconazole

Seven-day treatment with ketoconazole (200 mg per day), a potent inhibitor of CYP3A4, did not affect the steady-state pharmacokinetics of selegiline in subjects who received EMSAM 6 mg per 24 hours for 7 days and no differences in the pharmacokinetics of ketoconazole were observed [see Drug Interactions (7.4) and (7.5)].

Levothyroxine

In healthy subjects who had received EMSAM 6 mg per 24 hours for 10 days, single dose administration with levothyroxine (150 mcg) did not alter the pharmacokinetics of either selegiline or levothyroxine [see Drug Interactions (7.4) and (7.5)].

Olanzapine

In subjects who had received EMSAM 6 mg per 24 hours for 10 days, co-administration with olanzapine, a substrate for CYP1A2, CYP2D6, and possibly CYP2A6, did not affect the pharmacokinetics of selegiline or olanzapine [see Drug Interactions (7.4) and (7.5)].

Phenylpropanolamine (PPA)

In subjects who had received EMSAM 6 mg per 24 hours for 9 days, co-administration with PPA (25 mg every 4 hours for 24 hours) did not affect the pharmacokinetics of PPA. There was a higher incidence of significant blood pressure elevations with the co-administration of EMSAM and PPA than with PPA alone, suggesting a possible pharmacodynamic interaction [see Drug Interactions (7.4) and (7.5)].

Pseudoephedrine

EMSAM 6 mg per 24 hours for 10 days, co-administered with pseudoephedrine (60 mg, 3 times a day) did not affect the pharmacokinetics of pseudoephedrine. There were no clinically significant changes in blood pressure during pseudoephedrine administration alone, or in combination with EMSAM [see Drug Interactions (7.4) and (7.5)].

Risperidone

In subjects who had received EMSAM 6 mg per 24 hours for 10 days, co-administration with risperidone (2 mg per day for 7 days), a substrate for CYP2D6, did not affect the pharmacokinetics of selegiline or risperidone [see Drug Interactions (7.4) and (7.5)].

Warfarin

Warfarin is a substrate for CYP2C9 and CYP3A4 metabolism pathways. In healthy volunteers titrated with Coumadin® (warfarin sodium) to clinical levels of anticoagulation (INR of 1.5 to 2), co-administration with EMSAM 6 mg per 24 hours for 7 days did not affect the pharmacokinetics of the individual warfarin enantiomers. EMSAM did not alter the clinical pharmacodynamic effects of warfarin as measured by INR, Factor VII or Factor X levels [see Drug Interactions (7.4) and (7.5)].

13 NONCLINICAL TOXICOLOGY

13.1 Carcinogenesis, Mutagenesis, Impairment of Fertility

Carcinogenesis

In a dermal carcinogenicity study in CD-1 mice, selegiline (the drug substance of EMSAM) was administered daily for 2 years at the same skin site at dose levels of 20, 70, and 200 mg per kg per day (dissolved in acetone). The incidence of systemic tumors was not increased and the high dose provided systemic exposures to selegiline and its three metabolites in mice that were greater than 40 times the exposures in humans at the maximum recommended human dose (MRHD). The incidence of squamous cell carcinoma was slightly increased on treated skin of mice administered the high dose. This finding was associated with an increased incidence of epithelial hyperplasia, dyskeratosis/hyperkeratosis and inflammation.

In an oral carcinogenicity study in rats, selegiline given in the diet for 104 weeks was not carcinogenic up to the highest evaluable dose tested (3.5 mg per kg per day), which exposed rats to systemic levels of selegiline and its three metabolites that were comparable to those in humans at the MRHD.

Mutagenesis

Selegiline induced mutations and chromosomal damage when tested in the in vitro mouse lymphoma assay with and without metabolic activation. Selegiline was negative in the Ames assay, the in vitro mammalian chromosome aberration assay in human lymphocytes, and the in vivo oral mouse micronucleus assay.

Impairment of Fertility

A mating and fertility study was conducted in male and female rats at transdermal doses of 10, 30, and 75 mg per kg per day of selegiline (8, 24, and 60 times the maximum recommended human dose of EMSAM [12 mg per 24 hours] on a mg per m^2 basis). Slight decreases in sperm concentration and total sperm count were observed at the high dose; however, no significant adverse effects on fertility or reproductive performance were observed.

14 CLINICAL STUDIES

14.1 Major Depressive Disorder

The efficacy of EMSAM as a treatment for major depressive disorder was established in two placebo-controlled studies of 6 and 8 weeks duration in adult outpatients (ages 18 to 70 years) meeting DSM-IV criteria for major depressive disorder. In both studies, patients were randomized to double-blind treatment with EMSAM or placebo. The 6-week trial (N = 176) showed that EMSAM 6 mg per 24 hours was statistically significantly more effective than placebo on the 17-item Hamilton Depression Rating Scale (HAM-D) total score (Study 1 in Table 7). In an 8-week dose titration trial, depressed patients (N = 265), who received EMSAM or placebo at a starting dose of 6 mg per 24 hours, with possible increases to 9 mg per 24 hours or 12 mg per 24 hours based on clinical response, showed significant improvement compared with placebo on the primary outcome measure, the 28-item HAM-D total score (Study 2 in Table 7).

Table 7. Primary Efficacy Results from Short-Term Trials
Study Number [Primary Measure] | Treatment Group | Number of Patients | Mean Baseline Score (SD) | LS Mean Change from Baseline (SE) | Placebo-subtracted Difference [Difference (drug minus placebo) in least-squares mean change from baseline] (95% CI)
Study 1 | EMSAM (6 mg) | 89 | 22.9 (2.1) | -9.0 (0.8) | -2.5
[HAMD-17] | Placebo | 88 | 23.3 (2.9) | -6.5 (0.8) | (-4.6, -0.4)
Study 2 | EMSAM (6 to 12 mg) | 132 | 28.3 (3.7) | -10.9 (0.8) | -2.4
[HAMD-28] | Placebo | 133 | 28.5 (3.9) | -8.6 (0.8) | (-4.5, -0.3)
SD: standard deviation; SE: standard error; LS Mean: least-squares mean; CI: confidence interval.

In another trial (Study 3), 322 patients meeting DSM-IV criteria for major depressive disorder who had responded during an initial 10-week open-label treatment phase for about 25 days, on average, to EMSAM 6 mg per 24 hours were randomized either to continuation of EMSAM at the same dose (N = 159) or to placebo (N = 163) under double-blind conditions for observation of relapse. About 52% of the EMSAM-treated patients, as well as about 52% of the placebo-treated patients, had discontinued treatment by week 12 of the double-blind phase. Response during the open-label phase was defined as 17-item HAM-D total score less than 10 at either week 8 or 9 and at week 10 of the open-label phase. Relapse during the double-blind phase was defined as follows: (1) a 17-item HAM-D score of 14 or greater, (2) a CGI-S score of 3 or greater (with at least a 2-point increase from double-blind baseline), and (3) meeting DSM-IV criteria for major depressive disorder on two consecutive visits at least 11 days apart. In the double-blind phase, patients receiving continued EMSAM experienced a significantly longer time to relapse (Figure 2).

Figure 2. Kaplan-Meier Estimates of Cumulative Percent of Patients with Relapse (Study 3)

Figure 2. Kaplan-Meier Estimates of Cumulative Percent of Patients with Relapse (Study 3)

An examination of population subgroups did not reveal any clear evidence of differential responsiveness on the basis of age, gender, or race.

15 REFERENCES

1. Adapted from K.I. Shulman, S.E. Walker, Psychiatric Annals 2001; 31:378-384

16 HOW SUPPLIED/STORAGE AND HANDLING

How Supplied

EMSAM (selegiline transdermal system) is a transdermal system with the following strengths, sizes, color, backing film printing and presentation:

Features | Strengths
Features | 6 mg per 24 hours | 9 mg per 24 hours | 12 mg per 24 hours
EMSAM Size | 20 mg per 20 cm^2 | 30 mg per 30 cm^2 | 40 mg per 40 cm^2
Color | Translucent | Translucent | Translucent
Backing Film Printing | EMSAM® 6mg/24h | EMSAM® 9mg/24h | EMSAM® 12mg/24h
NDC number | NDC 49502-900-30 | NDC 49502-901-30 | NDC 49502-902-30
Presentation | Box of 30 transdermal systems | Box of 30 transdermal systems | Box of 30 transdermal systems

Storage and Handling

Store at 20° to 25° C (68° to 77° F). [See USP Controlled Room Temperature.] Do not store outside of the sealed pouch.

Apply immediately upon removal from the protective pouch. Discard used EMSAM in household trash in a manner that prevents accidental application or ingestion by children, pets or others.

17 PATIENT COUNSELING INFORMATION

See FDA-approved patient labeling (Medication Guide and Instructions for Use).

Advise patients and their caregivers about the benefits and risks associated with treatment with EMSAM and counsel them in its appropriate use. Advise patients and their caregivers to read the Medication Guide and assist them in understanding its contents. The complete text of the Medication Guide is reprinted at the end of this document.

Patients should be advised of the following issues and asked to alert their prescriber if these occur while taking EMSAM.

Suicide Risk: Advise patients and caregivers to look for the emergence of suicidal ideation and behavior, especially early during treatment and when the dose is adjusted up or down [see Boxed Warning and Warnings and Precautions (5.1)].

Tyramine Reactions: Patients should be advised that tyramine-rich foods and beverages should be avoided while on EMSAM 9 mg per 24 hours or EMSAM 12 mg per 24 hours, and for 2 weeks following discontinuation of EMSAM at these doses because of the risk of a tyramine reaction [see Warnings and Precautions (5.3), Drug Interactions (7.2), and Clinical Pharmacology (12.2)]. Patients should also be advised to avoid tyramine-containing nutritional supplements. Patients should be instructed to immediately report the occurrence of the following acute symptoms: severe headache, neck stiffness, heart racing or palpitations, or other sudden or unusual symptoms.

Concomitant Medication: Advise patients to inform their physicians if they are taking, or plan to take, any prescription or over-the-counter medications, including herbals, because of a potential for dangerous interactions. Instruct patients not to take EMSAM with medication that is contraindicated or within two weeks of stopping such medication (5 weeks for fluoxetine). Contraindicated medication should not be started within two weeks of stopping EMSAM [see Contraindications (4)].

Psychomotor Performance: EMSAM has not been shown to impair psychomotor performance; however, any psychoactive drug may potentially impair judgment, thinking, or motor skills. Patients should be cautioned about operating hazardous machinery, including automobiles, until they are reasonably certain that EMSAM therapy does not impair their ability to engage in such activities.

Alcohol: Patients should be told that, although EMSAM has not been shown to increase the impairment of mental and motor skills caused by alcohol, the concomitant use of EMSAM and alcohol in depressed patients is not recommended.

Pediatrics: Advise patients that EMSAM must not be used in children less than 12 years of age because of an increased risk of severe increases in blood pressure. Also, patients should be advised that EMSAM is not recommended for use in pediatric patients ages 12 to 17 years [see Use in Specific Populations (8.4)].

Pregnancy: Advise the pregnant woman about the potential risk to the fetus [see Use in Specific Populations (8.1)].

Lactation: Advise a woman that breastfeeding is not recommended during treatment with EMSAM treatment and for 5 days after the final dose [see Use in Specific Populations (8.2)].

How to Use EMSAM

Detailed Instructions are provided in the Medication Guide. Prescribers should instruct patients on the following:

- EMSAM should be applied to dry, intact skin on the upper torso (below the neck and above the waist), upper thigh or the outer surface of the upper arm. A new application site should be selected with each new transdermal system to avoid re-application to the same site on consecutive days. Transdermal systems should be applied at approximately the same time each day.
- Apply the transdermal system to an area of skin that is not hairy, oily, irritated, broken, scarred or calloused. Do not place the transdermal system where your clothing is tight, which could cause the transdermal system to rub off.
- After you have selected the site for your transdermal system, wash the area gently and thoroughly with soap and warm water. Rinse until all soap is removed. Dry the area with a clean dry towel.
- Just before you apply the transdermal system, remove it from the pouch by tearing at the notches (do not use scissors). Remove half of the release liner and throw it away. Try not to touch the exposed side (sticky side) of the transdermal system, because the medicine could come off on your fingers.
- Press the sticky side of the transdermal system firmly against the skin site that was just washed and dried. Remove the second half of the release liner and press the remaining sticky side firmly against your skin. Make sure that the transdermal system is flat against the skin (there should be no bumps or folds in the transdermal system) and is sticking securely. Be sure the edges are stuck to the skin surface.
- After you have applied the transdermal system, wash your hands thoroughly with soap and water to remove any medicine that may have gotten on them. Do not touch your eyes until after you have washed your hands.
- After 24 hours, remove your transdermal system slowly and carefully to avoid damaging your skin.
- If the transdermal system is too sticky on your skin, and you need something to help you remove it:
  - Gently wash the area with warm water and mild soap.
  - A small amount of oil-based product (petroleum jelly, olive oil, or mineral oil) may be needed to help remove the transdermal system. Gently apply and spread the oil underneath the transdermal system edges.
  - Apply an oil-based product or lotion to your skin if any adhesive (glue) remains after you remove your transdermal system. This will gently loosen and remove any adhesive that is left over.
- Fold the used EMSAM transdermal system in half and press it together firmly so that the sticky side sticks to itself.
- Safely throw away the folded transdermal system in a container with a lid right away so that children and pets cannot reach it.
- Safely throw away any unused EMSAM transdermal systems that are left over from the prescription as soon as they are no longer needed.
- Wash your hands with soap and water.
- If your transdermal system falls off, apply a new transdermal system to a new site and resume your previous schedule.
- Only one EMSAM transdermal system should be worn at a time.
- Do not cut the EMSAM transdermal system into smaller portions.

The brands listed are trademarks of their respective owners.

MEDICATION GUIDE

EMSAM® [EM sam]
(selegiline transdermal system)

What is the most important information I should know about EMSAM?

1. Antidepressant medicines may increase suicidal thoughts or actions in some children, teenagers, and young adults within the first few months of treatment.
2. Depression and other serious mental illnesses are the most important causes of suicidal thoughts and actions. Some people may have a particularly high risk of having suicidal thoughts or actions. These include people who have or have a family history of bipolar illness (also called manic-depressive illness) or suicidal thoughts or actions. How can I watch for and try to prevent suicidal thoughts and actions?
  1. Pay close attention to any changes, especially sudden changes in mood, behavior, thoughts, or feelings. This is very important when an antidepressant medicine is started or when the dose is changed.
  2. Call the healthcare provider right away to report new or sudden changes in mood, behavior, thoughts, or feelings.
  3. Keep all follow-up visits with your healthcare provider as scheduled. Call the healthcare provider between visits as needed, especially if you have concerns about symptoms.

Call a healthcare provider right away if you have any of the following symptoms, especially if they are new, worse, or worry you:

- thoughts about suicide or dying
- attempts to commit suicide
- new or worse depression
- new or worse anxiety
- feeling agitated, restless, angry or irritable
- panic attacks
- trouble sleeping

- new or worse irritability
- acting aggressive, being angry or violent
- acting on dangerous impulses
- an extreme increase in activity or talking (mania)
- other unusual changes in behavior or mood

3. EMSAM is not for children less than 12 years of age. EMSAM may cause a severe increase in blood pressure in children less than 12 years of age.

What is EMSAM?

EMSAM is a prescription medicine used to treat a certain type of depression called Major Depressive Disorder (MDD). EMSAM belongs to the class of medicines known as monoamine oxidase inhibitors (MAOI). EMSAM is a transdermal system (patch) you apply to your skin.

It is important to talk with your healthcare provider about the risks of treating depression and also the risk of not treating it. You should discuss all treatment choices with your healthcare provider.

Talk to your healthcare provider if you do not think that your condition is getting better with EMSAM treatment.

Who should not use EMSAM?

Using EMSAM with certain antidepressants and certain pain, cold and cough symptom medicines may cause a potentially life-threatening problem called serotonin syndrome (See “What are the possible side effects of EMSAM?”).

Do not use EMSAM if you:

- take certain medicines including:
  - selective serotonin reuptake inhibitors (SSRIs) such as fluoxetine, sertraline, or paroxetine
  - serotonin and norepinephrine reuptake inhibitors (SNRI) such as venlafaxine or duloxetine
  - clomipramine or imipramine (tricyclic antidepressants)
  - meperidine, tramadol, methadone, pentazocine, propoxyphene (opioid medicines)
  - dextromethorphan
  - carbamazepine
- are less than 12 years of age
- have a tumor on your adrenal gland called a pheochromocytoma

Ask your healthcare provider or pharmacist if you are not sure if you take these medicines.

Before you use EMSAM, tell your healthcare provider about all of your medical conditions, including if you:

- have high blood pressure
- have mania or bipolar disorder (manic depression)
- have or had seizures or convulsions
- drink alcohol
- have any other medical conditions
- are pregnant or plan to become pregnant. EMSAM may harm your unborn baby.
- are breastfeeding or plan to breastfeed. It is not known if EMSAM passes into your breast milk. Do not breastfeed during treatment with EMSAM and for 5 days after the final dose. Talk to your healthcare provider about the best way to feed your baby if you use EMSAM.

Tell your doctor about all the medicines you take including prescription and over-the-counter medicines, vitamins, and herbal supplements. EMSAM and some medicines may interact with each other, may not work as well, or may cause serious side effects when taken together.

Especially tell your healthcare provider if you take:

- other medicines to treat depression (antidepressants) including other MAOI medicines
- decongestant medicines to treat cold or cough symptoms
- over-the-counter diet pills or herbal weight-loss products
- any herbal or dietary supplement that contains tyramine
- medicines called stimulants or uppers (amphetamines)
- buspirone, an anxiety medicine

Some of these medicines need to be stopped for up to 5 weeks before you can start using EMSAM and for 2 weeks after you stop using EMSAM.

Ask your healthcare provider or pharmacist if you are not sure if you take these medicines.

Know the medicines you take. Keep a list of them to show your healthcare provider or pharmacist when you get a new medicine.

How should I use EMSAM?

- Read the “Instructions for Use” at the end of this Medication Guide for information about the right way to use EMSAM.
- Use EMSAM exactly as your healthcare provider tells you to use it.
- Use only 1 patch at a time.
- Apply your patch right after you open the sealed pouch.
- Change your patch 1 time each day at the same time each day. Choose a time of day that works best for you.
- Your healthcare provider may need to change your dose of EMSAM until it is the right dose for you.
- If you use too much EMSAM (overdose) you may have the following symptoms:

- drowsiness
- irritable
- severe headache
- your head, neck and spine arch backwards
- fast or irregular pulse
- blood circulation problem
- high fever

- dizziness
- hyperactive
- seeing things that are not there
- seizures
- high blood pressure
- chest pain
- sweating

- fainting
- agitated
- stiff jaw
- coma
- low blood pressure
- trouble breathing
- cool, clammy skin

If you have any of these symptoms of EMSAM overdosage, remove your patch right away and call your healthcare provider or go to the nearest hospital emergency room right away. It may take up to 12 hours before you have these symptoms, and they may be worse 24 to 48 hours after you apply your EMSAM patch.

What should I avoid while using EMSAM?

- Avoid exposing the EMSAM application site to external sources of direct heat, such as heating pads or electric blankets, heat lamps, saunas, hot tubs, heated water beds, and prolonged direct sunlight.
- Do not eat foods or drink beverages that contain high amounts of tyramine while using EMSAM 9 mg or EMSAM 12 mg or for 2 weeks after you stop using EMSAM 9 mg or EMSAM 12 mg. Continue to avoid tyramine-rich foods or beverages for 2 weeks after a dose reduction to EMSAM 6 mg.
- If you start and continue EMSAM 6 mg you do not need to make any diet changes.
- The table below lists foods and drinks you should avoid while you use EMSAM 9 mg and EMSAM 12 mg.

Type of Food and Drink

Foods and drinks you should avoid that contain Tyramine

Meat, Poultry, and Fish

- air dried, aged and fermented meats, sausages and salamis
- pickled herring
- any spoiled or improperly stored meat, poultry, and fish. These are foods that have a change in color, odor, or become moldy.
- spoiled or improperly stored animal livers

Vegetables

- broad bean pods (fava bean pods)

Dairy (milk products)

- aged cheeses

Drinks

- all tap beers and other beers that have not been pasteurized

Other

- concentrated yeast extract (such as Marmite)
- sauerkraut
- most soybean products (including soy sauce and tofu)
- over-the-counter supplements containing tyramine

- All foods you eat must be fresh or properly frozen.
- Avoid foods when you do not know how those foods should be stored.
- Ask your healthcare provider if you are not sure if certain foods and drinks contain tyramine.
- Do not drive, operate heavy machinery or do other dangerous activities until you know how EMSAM affects you.
- You should not drink alcohol while using EMSAM.

What are the possible side effects of EMSAM?

EMSAM may cause serious side effects, including:

- See “What is the most important information I should know about EMSAM?”
- serotonin syndrome. A potentially life-threatening problem called serotonin syndrome can happen when you use EMSAM while you take certain medicines called MAOIs. Symptoms of serotonin syndrome include:

- agitation
- coma
- dizziness
- fever
- stiff muscles
- nausea

- seeing things that are not there (hallucinations)
- rapid pulse
- sweating
- seizures
- muscle twitching
- vomiting

- confusion
- low blood pressure
- flushing
- tremors
- become unstable
- diarrhea

If you suddenly have these symptoms, stop using EMSAM immediately by removing the patch and go to the nearest hospital emergency room right away.

- a sudden, severe increase in blood pressure (hypertensive crisis). A hypertensive crisis can happen when you eat certain foods and drink certain beverages while you use EMSAM. A hypertensive crisis can lead to stroke and death.
  See “What should I avoid while using EMSAM?”
  A hypertensive crisis can also happen if you use EMSAM with certain other medicines. See “Who should not use EMSAM?”
  Symptoms of a hypertensive crisis include:

- sudden, severe headache
- vomiting
- a fast heartbeat (palpitations) or a change in the way your heart beats
- the pupils in your eyes increase in size
- fast or slow heart beat with chest pain

- nausea
- stiff or sore neck
- excessive sweating, sometimes with fever or cold clammy skin
- light bothers your eyes
- bleeding in your brain

If you suddenly have these symptoms, go to the nearest hospital emergency room right away.
2. mania or hypomania (manic episodes) in people who have a history of mania. Symptoms of manic episodes include:

- greatly increased energy
- severe problems sleeping
- racing thoughts

- reckless behavior
- unusually grand ideas
- excessive happiness or irritability

- talking more or faster than usual

The most common side effects of EMSAM include:

- a skin reaction where the patch is placed. You may see mild redness at the site when a patch is removed. This redness should go away within several hours after removing the patch. If irritation or itching continues, tell your healthcare provider.
- headache
- trouble sleeping (insomnia)
- diarrhea
- dry mouth
- indigestion
- rash
- sore throat
- sinus infection

These are not all the possible side effects of EMSAM. Call your doctor for medical advice about side effects. You may report side effects to FDA at 1-800-FDA-1088.

How should I store EMSAM?

- Store EMSAM at room temperature between 68°F to 77°F (20°C to 25°C).
- Store EMSAM in the sealed pouch it comes in until you are ready to use it.
- Keep EMSAM and all medicines out of the reach of children.

General information about the safe and effective use of EMSAM.

Medicines are sometimes prescribed for purposes other than those listed in a Medication Guide. Do not use EMSAM for a condition for which it was not prescribed. Do not give EMSAM to other people, even if they have the same symptoms that you have. It may harm them. You can ask your healthcare provider or pharmacist for information about EMSAM that is written for health professionals.

What are the ingredients in EMSAM?

Active Ingredient: selegiline

Inactive Ingredients: acrylic adhesive, ethylene vinyl acetate, polyethylene, polyester, polyurethane, and silicone coated polyester

Distributed by: Mylan Specialty L.P., Morgantown, WV 26505 U.S.A.

Manufactured for:
Somerset Pharmaceuticals, Inc.
Morgantown, WV 26505 U.S.A.

For more information, go to www.EMSAM.com or call 1-800-395-3376.

This Medication Guide has been approved by the U.S. Food and Drug Administration
Issued: 5/2020

Instructions for Use

EMSAM® [EM sam]
(selegiline transdermal system)

Step 1. Where to apply EMSAM

- Place your EMSAM transdermal system (patch) on one of the following areas (sites) on your body. See Figure A.

Figure A

- EMSAM should be applied to dry, intact skin on the upper torso (below the neck and above the waist), upper thigh or the outer surface of the upper arm. Clothing and movement may make your patch rub off.
- Choose a new site each time you change your patch. Do not use the same site 2 days in a row.

Step 2. Before you apply EMSAM

- Make sure the area on your skin where you apply your patch:
  - is freshly washed with soap and warm water, then dried with a towel
  - does not have any powder, oil or lotion
  - does not have any cuts or irritation, including rashes, swelling, redness, or other skin problems
  - is not hairy, scarred or calloused

Step 3. How to apply EMSAM

- Remove EMSAM from its sealed pouch by tearing at the notches (do not use scissors). Pull the pouch open. See Figure B.

Figure B

- Look at the patch to make sure it is not damaged. The patch should separate easily from the release liner. Throw away the patch if the release liner is hard to remove.
- Do not keep or store your EMSAM outside of the sealed pouch. Do not cut your EMSAM into smaller pieces.
- The EMSAM patch has three layers. See Figures C and D.

Figure C Figure D

Layers:

  - Release liner: The release liner is the layer that you remove before you put the patch on. See Figure C.
  - Adhesive with medicine: The adhesive with medicine is the layer that sticks to your skin. See Figure C.
  - Outside backing: The outside backing is the layer you see after you put the patch on your skin. See Figure D.
- Apply the patch right away after you remove the patch from its sealed pouch.
- Hold the patch with the release liner facing you.
- Gently peel half of the release liner off the patch and throw it away. See Figure E.

Figure E

- Avoid touching the sticky side of the patch with your fingers. If you accidently touch the sticky side of the patch, wash your hands right away so the medicine does not go into the skin on your hands.
- Using the other half of the release liner as a handle, apply the sticky side of the patch to your selected area. See Figure F.

Figure F

- Hold an edge of the remaining half of the release liner and slowly peel it off. See Figure G.

Figure G

- After the release liner is removed, there should not be any adhesive sticking to the liner.
- Using your fingers and palm of your hand, press the entire patch firmly into place against your skin. See Figure H.

Figure H

- Make sure the patch firmly sticks to your skin.
- Gently rub the edges of your patch with your fingers to make sure the patch sticks to your skin.
- Wash your hands well with soap and water after you apply your patch to remove any medicine. Do not touch your eyes until after you have washed your hands.
- If the patch becomes loose, press it back in place. If your EMSAM patch falls off, apply a new EMSAM patch to a new site and follow your normal schedule for changing patches.
- If you forget to change your patch after 24 hours, remove the old patch. Put on a new patch in a different area and continue to follow your normal schedule for changing patches.

Step 4. Removing and disposing of your patch

- After 24 hours, remove your patch slowly and carefully to avoid damaging your skin.
- If the patch is too sticky on your skin and you need something to help you remove it:
  - Gently wash the area with warm water and mild soap.
  - A small amount of oil-based product (petroleum jelly, olive oil, or mineral oil) may be needed to help remove the patch. Gently apply and spread the oil underneath the patch edges.
  - Apply an oil-based product or lotion to your skin if any adhesive (glue) remains after you remove your patch. This will gently loosen and remove any adhesive that is left over.
  - If you still cannot easily remove the patch, ask your doctor or pharmacist about what to do for this problem.
- Fold the used EMSAM patch in half and press it together firmly so that the sticky side sticks to itself.
- Safely throw away the folded patch in a container with a lid right away so that children and pets cannot reach it.
- Safely throw away any unused EMSAM patches that are left over from the prescription as soon as they are no longer needed.
- To safely throw away the patches:
  - Remove the leftover patches from their protective pouches and remove the release liners.
  - Fold the patches in half with the sticky sides together and throw the patches away in a container with a lid.
- Wash your hands with soap and water.

This Instructions for Use has been approved by the U.S. Food and Drug Administration.

DISTRIBUTED BY:
Mylan Specialty L.P.
Morgantown, WV 26505 U.S.A.

MANUFACTURED FOR:
Somerset Pharmaceuticals, Inc.
Morgantown, WV 26505 U.S.A.

Revised: 5/2020
EMSAM:PIR15/EMSAM:PLR15

PRINCIPAL DISPLAY PANEL - 6 mg/24 h

NDC-49502-900-30

EACH UNIT DOSE PACKAGE IS NOT CHILD RESISTANT
Rx only

EMSAM®
(selegiline transdermal system)
6 mg/24 h

FOR TRANSDERMAL USE ONLY

Patient: Read enclosed Medication Guide.

Pharmacist: Dispense with enclosed
Medication Guide.

30 TRANSDERMAL
SYSTEMS

INSTRUCTIONS FOR APPLICATION

1. Select and prepare an appropriate site on the upper chest or back (below the neck and above the waist), the upper thigh, or the outer surface of the upper arm, as directed in the enclosed Medication Guide.

2. Bend both sides of the clear peelable liner. Peel off one strip only of the clear liner. Avoid touching the sticky side of the transdermal system.

3. Apply sticky side of the transdermal system to the chosen skin site. Remove remaining strip, gently roll remaining part onto skin, and press transdermal system firmly in place with the tips of your fingers.

For more detailed instructions, read enclosed Medication Guide.

Dosage: Apply one (1) transdermal system every 24 hours. Read enclosed Medication Guide.

Each transdermal system has a release rate of 6 mg selegiline per 24 hour period. Wear only one transdermal system at a time.

Store at 20° to 25°C (68° to 77°F). [See USP Controlled Room Temperature.]

Dist. by
Mylan Specialty L.P.
Morgantown, WV 26505 U.S.A.

Mfd. for
Somerset Pharmaceuticals, Inc.
Morgantown, WV 26505 U.S.A.

Rx only

S033:93:30C:R10

PRINCIPAL DISPLAY PANEL - 9 mg/24 h

NDC-49502-901-30

EACH UNIT DOSE PACKAGE IS NOT CHILD RESISTANT
Rx only

EMSAM®
(selegiline transdermal system)
9 mg/24 h

Important: Do not eat certain foods.
Read enclosed Medication Guide.

FOR TRANSDERMAL USE ONLY

Pharmacist: Dispense with enclosed
Medication Guide.

30 TRANSDERMAL
SYSTEMS

INSTRUCTIONS FOR APPLICATION

1. Select and prepare an appropriate site on the upper chest or back (below the neck and above the waist), the upper thigh, or the outer surface of the upper arm, as directed in the enclosed Medication Guide.

2. Bend both sides of the clear peelable liner. Peel off one strip only of the clear liner. Avoid touching the sticky side of the transdermal system.

3. Apply sticky side of the transdermal system to the chosen skin site. Remove remaining strip, gently roll remaining part onto skin, and press transdermal system firmly in place with the tips of your fingers.

For more detailed instructions, read enclosed Medication Guide.

Dosage: Apply one (1) transdermal system every 24 hours. Read enclosed Medication Guide.

Each transdermal system has a release rate of 9 mg selegiline per 24 hour period. Wear only one transdermal system at a time.

Store at 20° to 25°C (68° to 77°F). [See USP Controlled Room Temperature.]

Dist. by
Mylan Specialty L.P.
Morgantown, WV 26505 U.S.A.

Mfd. for
Somerset Pharmaceuticals, Inc.
Morgantown, WV 26505 U.S.A.

Rx only

S044:93:30C:R10

PRINCIPAL DISPLAY PANEL - 12 mg/24 h

NDC-49502-902-30

EACH UNIT DOSE PACKAGE IS NOT CHILD RESISTANT
Rx only

EMSAM®
(selegiline transdermal system)
12 mg/24 h

Important: Do not eat certain foods.
Read enclosed Medication Guide.

FOR TRANSDERMAL USE ONLY

Pharmacist: Dispense with enclosed
Medication Guide.

30 TRANSDERMAL
SYSTEMS

INSTRUCTIONS FOR APPLICATION

1. Select and prepare an appropriate site on the upper chest or back (below the neck and above the waist), the upper thigh, or the outer surface of the upper arm, as directed in the enclosed Medication Guide.

2. Bend both sides of the clear peelable liner. Peel off one strip only of the clear liner. Avoid touching the sticky side of the transdermal system.

3. Apply sticky side of the transdermal system to the chosen skin site. Remove remaining strip, gently roll remaining part onto skin, and press transdermal system firmly in place with the tips of your fingers.

For more detailed instructions, read enclosed Medication Guide.

Dosage: Apply one (1) transdermal system every 24 hours. Read enclosed Medication Guide.

Each transdermal system has a release rate of 12 mg selegiline per 24 hour period. Wear only one transdermal system at a time.

Store at 20° to 25°C (68° to 77°F). [See USP Controlled Room Temperature.]

Dist. by
Mylan Specialty L.P.
Morgantown, WV 26505 U.S.A.

Mfd. for
Somerset Pharmaceuticals, Inc.
Morgantown, WV 26505 U.S.A.

Rx only

S055:93:30C:R10